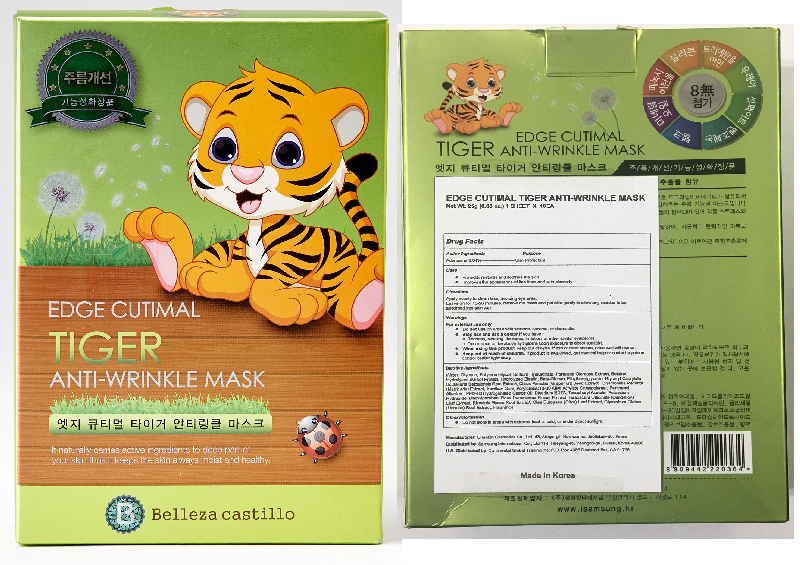 DRUG LABEL: Edge Cutimal Tiger Anti-Wrinkle Mask
NDC: 70889-200 | Form: PATCH
Manufacturer: Oneskin Cosmetics Co., Ltd.
Category: otc | Type: HUMAN OTC DRUG LABEL
Date: 20200317

ACTIVE INGREDIENTS: ADENOSINE 0.01 g/25 g
INACTIVE INGREDIENTS: WATER; BUTYLENE GLYCOL; HYALURONATE SODIUM; GLYCERIN; ROSA DAMASCENA FLOWERING TOP; ETHYLHEXYLGLYCERIN; MATRICARIA CHAMOMILLA WHOLE; TARAXACUM OFFICINALE LEAF; RHODIOLA ROSEA ROOT; OLEA EUROPAEA LEAF; SCUTELLARIA BAICALENSIS ROOT; PORTULACA OLERACEA WHOLE; HYDROLYZED WHEAT PROTEIN (ENZYMATIC, 3000 MW); CITRUS PARADISI SEED; EDETATE DISODIUM; .ALPHA.-TOCOPHEROL ACETATE; POTASSIUM HYDROXIDE; METHYLPARABEN; GLYCYRRHIZA GLABRA WHOLE; PEG-60 HYDROGENATED CASTOR OIL; XANTHAN GUM; PANTHENOL; ALLANTOIN; GLYCERYL CAPRYLATE/CAPRATE; BETAINE

ACTIVE INGREDIENT

Adenosine 0.04%

PURPOSE

Skin Protectant

INDICATIONS AND USAGE

- Protects, restores and soothes the skin
- Improves the appearance of fine lines and skin elasticity

DOSAGE AND ADMINISTRATION

Apply evenly to clean face, avoiding eye area.

Leave on for 15-20 minutes, remove the mask and pat skin gently to allow any residue to be absorbed into skin well.

WARNINGS

For external use only

- Do not use on areas with wounds, eczema, or dermatitis.
- Stop use and ask a doctor if you have

a. Redness, swelling, itchiness, irritation, or other similar symptoms.
b. Occurrence of the above symptoms upon exposure to direct sunlight.

- When using this product, keep out of eyes. If eye contact occurs, rinse well with water.

Keep out of reach of children. If product is swallowed, get medical help or contact a poison control center right away

INACTIVE INGREDIENT

Water, Glycerin, Butylene Glycol, Sodium Hyaluronate, Portulaca Oleracea Extract, Betaine, Hydrolyzed Wheat Protein, Hydrolyzed Elastin, Beta-Glucan, Ethylhexylglycerin, Glyceryl Caprylate, Scutellaria Baicalensis Root Extract, Citrus Paradisi (Grapefruit) Seed Extract, Chamomilla Recutita (Matricaria) Extract, Xanthan Gum, Acrylates/C10-30 Alkyl Acrylate Crosspolymer, Panthenol, Allantoin, PEG-60 Hydrogenated Castor Oil, Disodium EDTA, Tocopheryl Acetate, Potassium Hydroxide, Methylparaben, Rosa Damascena Flower Extract, Taraxacum Officinale (Dandelion) Leaf Extract, Rhodiola Rosea Root Extract, Olea Europaea (Olive) Leaf Extract, Glycyrrhiza Glabra (Licorice) Root Extract, Fragrance.

OTHER SAFETY INFORMATION

Do not store in areas with extreme heat or cold, or under direct sunlight.